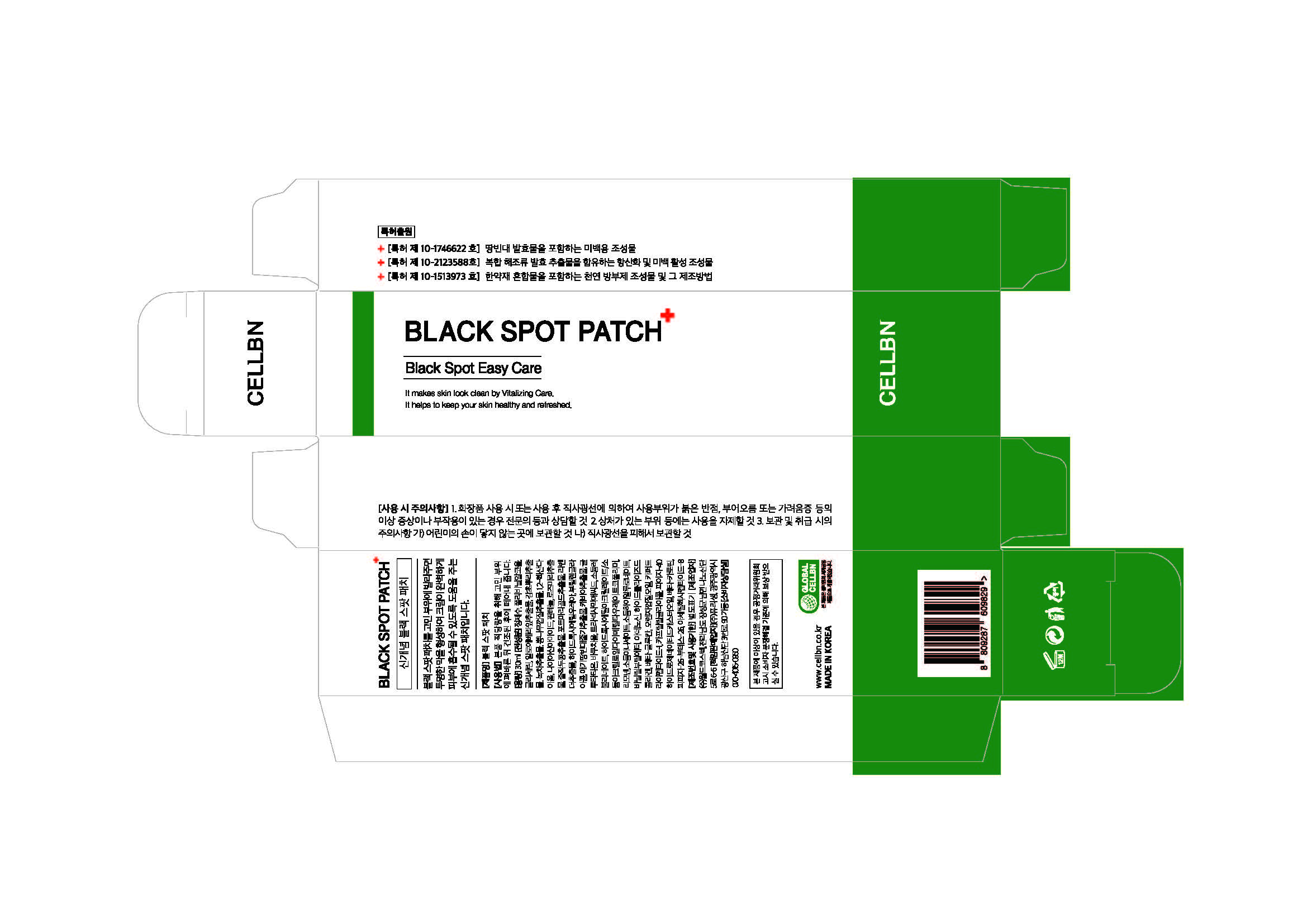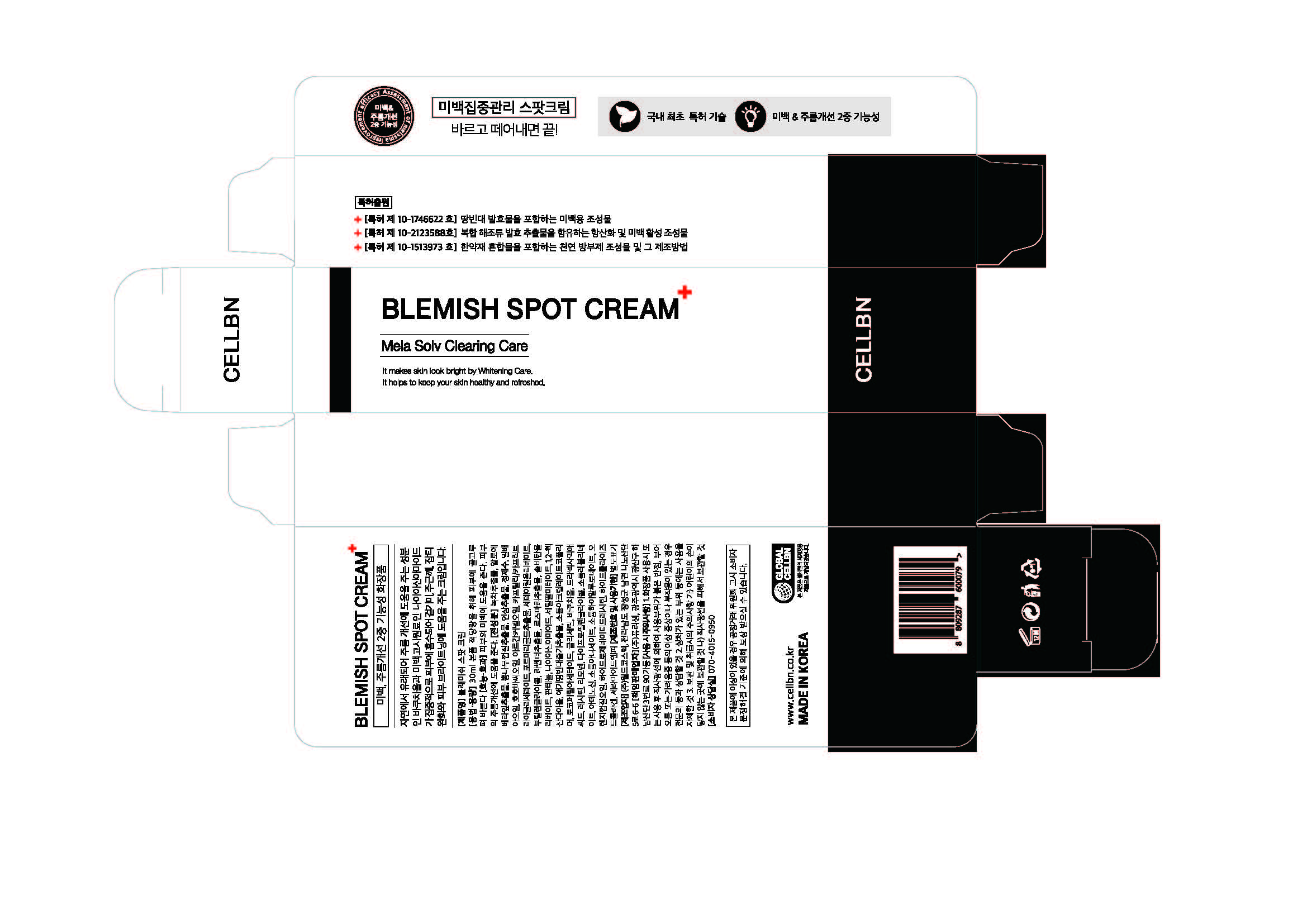 DRUG LABEL: CELLBN BLEMISH SPOTCREAM AND BLACK SPOTPATCH
NDC: 71450-0012 | Form: KIT | Route: TOPICAL
Manufacturer: WORLDCOSTEC.CO.,LTD
Category: otc | Type: HUMAN OTC DRUG LABEL
Date: 20220530

ACTIVE INGREDIENTS: ADENOSINE 0.015 g/30 mL; NIACINAMIDE 0.6 g/30 mL; ADENOSINE 0.015 g/30 mL; NIACINAMIDE 0.6 g/30 mL
INACTIVE INGREDIENTS: WATER; BUTYLENE GLYCOL; GLYCERIN; 1,2-HEXANEDIOL; WATER; BUTYLENE GLYCOL; GLYCERIN; 1,2-HEXANEDIOL

ACTIVE INGREDIENT

Glycerin, Adenosine

INACTIVE INGREDIENT

Water, Butylene Glycol, Glycerin, 1,2-Hexanediol, etc.

PURPOSE

Skin Protectant - Whitening, Anti-Wrinkle

Keep out of reach of the children

INDICATIONS AND USAGE

Please follow the contents of the label

WARNINGS

1. Do not use in the following cases(Eczema and scalp wounds)
2.Side Effects
1)Due to the use of this druf if rash, irritation, itching and symptopms of hypersnesitivity occur dicontinue use and consult your phamacisr or doctor
3.General Precautions
1)If in contact with the eyes, wash out thoroughty with water If the symptoms are servere, seek medical advice immediately
2)This product is for exeternal use only. Do not use for internal use
4.Storage and handling precautions
1)If possible, avoid direct sunlight and store in cool and area of low humidity
2)In order to maintain the quality of the product and avoid misuse
3)Avoid placing the product near fire and store out in reach of children

DOSAGE AND ADMINISTRATION

for external use only